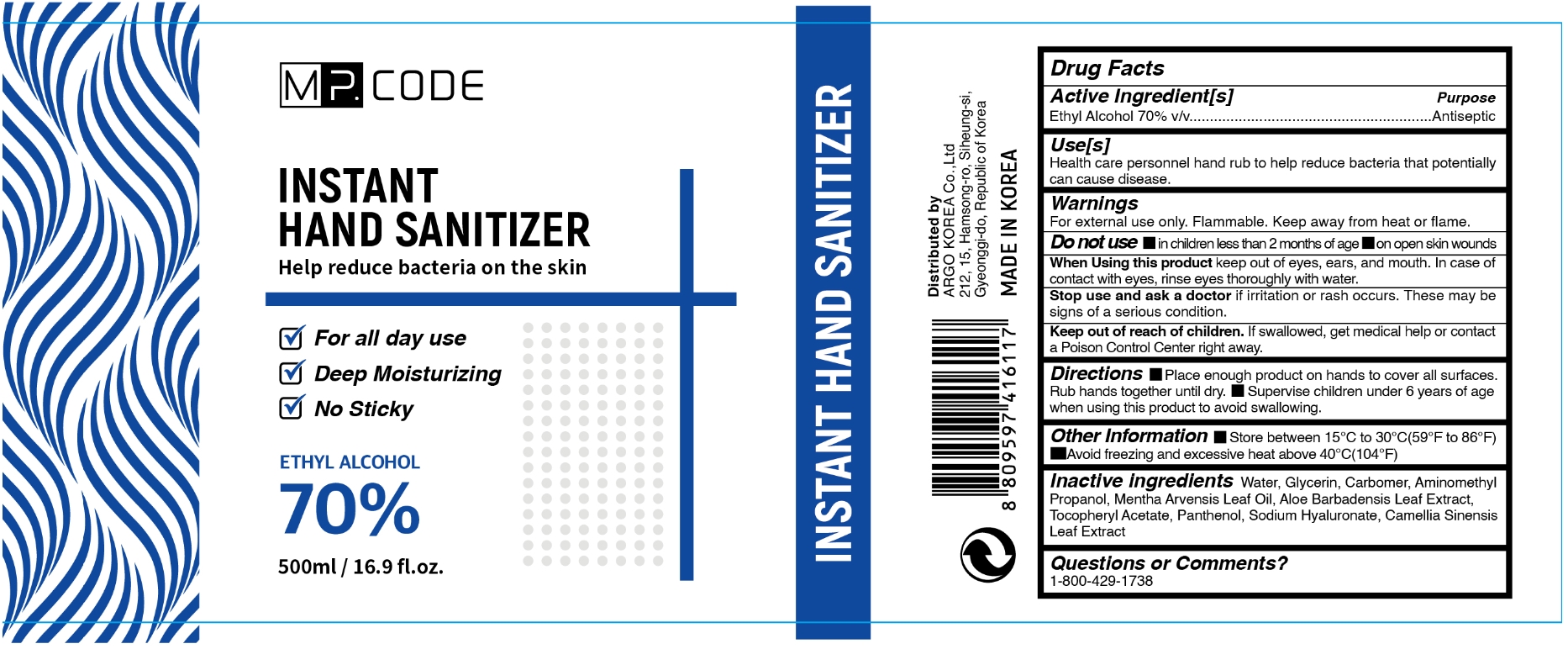 DRUG LABEL: MP. CODE INSTANT HAND SANITIZER 500ml
NDC: 76887-101 | Form: GEL
Manufacturer: ARGO KOREA Co., Ltd
Category: otc | Type: HUMAN OTC DRUG LABEL
Date: 20200528

ACTIVE INGREDIENTS: ALCOHOL 70 mL/100 mL
INACTIVE INGREDIENTS: WATER; ALOE VERA LEAF; PANTHENOL; AMINOMETHYLPROPANOL; CARBOMER 940; MENTHA ARVENSIS LEAF OIL; .ALPHA.-TOCOPHEROL ACETATE; HYALURONATE SODIUM; GREEN TEA LEAF; GLYCERIN

MP. CODE INSTANT HAND SANITIZER 70% 500ml

Active Ingredient(s)

Ethyl Alcohol 70% v/v. Purpose: Antiseptic

Purpose

Antiseptic, Hand Sanitizer

Use

Health care personnel hand rub to help reduce bacteria that potentially can cause disease.

Warnings

For external use only. Flammable. Keep away from heat or flame

Do not use

- in children less than 2 months of age
- on open skin wounds

When using

When using this product keep out of eyes, ears, and mouth. In case of contact with eyes, rinse thoroughly with water.

Stop use

Stop use and ask a doctor if irritation or rash occurs. These may be signs of a serious condition.

Keep out of reach of children. If swallowed, get medical help or contact a Poison Control Center right away.

Directions

- Place enough product on hands to cover all surfaces. Rub hands together until dry.
- Supervise children under 6 years of age when using this product to avoid swallowing.

Other information

- Store between 15-30C (59-86F)
- Avoid freezing and excessive heat above 40C (104F)

Inactive ingredients

Water, Glycerin, Carbomer, Aminomethyl Propanol, Mentha Arvensis Leaf Oil. Aloe Barbadensis Leaf Extract, Tocopheryl Acetate, Panthenol, Sodium Hyaluronate, Camellia Sinensis Leaf Extract

Questions or Comments?

1-800-429-1738

Package Label - Principal Display Panel

MP.CODE

INSTANT

HAND SANITIZER
Help reduce bacteria on the skin
For all day use
Deep Moisturizing

Refreshing Aloe
ETHYL ALCOHOL
70%
500ml / 16.9fl.oz.